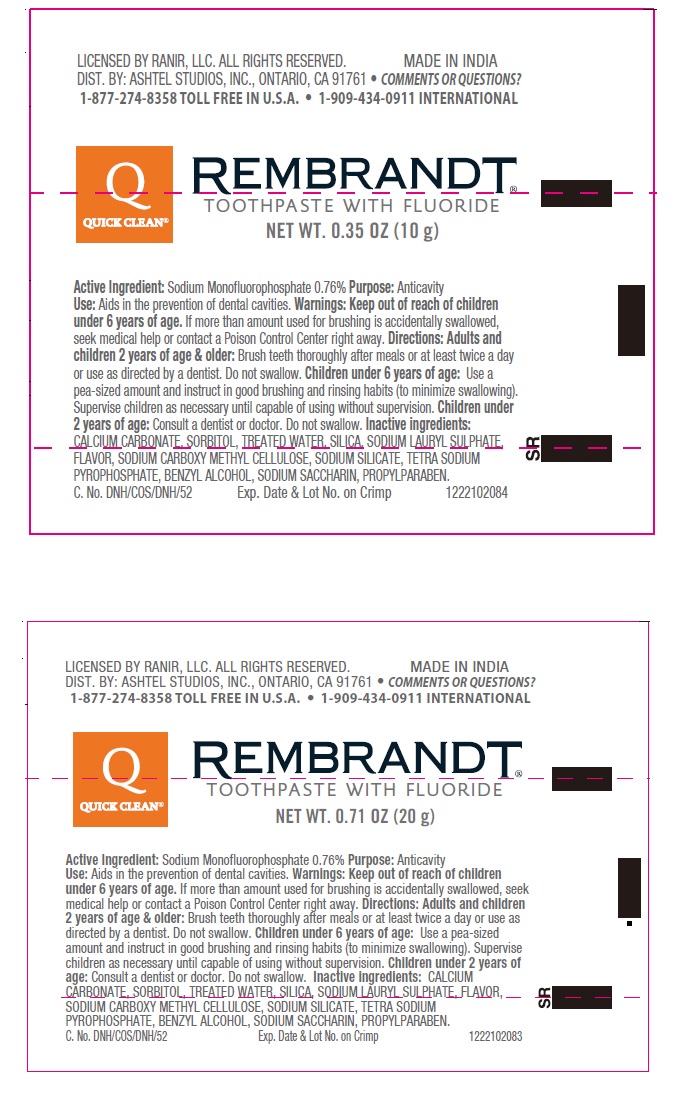 DRUG LABEL: Rembrandt
NDC: 70108-031 | Form: PASTE, DENTIFRICE
Manufacturer: Ashtel Studios, Inc
Category: otc | Type: HUMAN OTC DRUG LABEL
Date: 20191209

ACTIVE INGREDIENTS: SODIUM MONOFLUOROPHOSPHATE 0.76 g/100 g
INACTIVE INGREDIENTS: CALCIUM CARBONATE; SORBITOL; WATER; SILICON DIOXIDE; SODIUM LAURYL SULFATE; CARBOXYMETHYLCELLULOSE SODIUM, UNSPECIFIED FORM; SODIUM SILICATE; SODIUM PYROPHOSPHATE; BENZYL ALCOHOL; SACCHARIN SODIUM; PROPYLPARABEN

REMBRANDT® TOOTHPASTE WITH FLUORIDE

Active Ingredient: Sodium Monofluorophosphate 0.76%

Purpose: Anticavity

INDICATIONS AND USAGE

Use: Aids in the prevention of dental cavities.

WARNINGS

KEEP OUT OF REACH OF CHILDREN

Warnings: Keep out of reach of children under 6 years of age. If more than amount used for brushing is accidentally swallowed,
seek medical help or contact a Poison Control Center right away.

DOSAGE AND ADMINISTRATION

Directions: Adults and children 2 years of age & older: Brush teeth thoroughly after meals or at least twice a day or use as directed by a dentist. Do not swallow. Children under 6 years of age: Use a pea-sized amount and instruct in good brushing and rinsing habits (to minimize swallowing). Supervise children as necessary until capable of using without supervision. Children under 2 years of age: Consult a dentist or doctor. Do not swallow.

INACTIVE INGREDIENT

Inactive ingredients: CALCIUM CARBONATE, SORBITOL, TREATED WATER, SILICA, SODIUM LAURYL SULPHATE, FLAVOR, SODIUM CARBOXY METHYL CELLULOSE, SODIUM SILICATE, TETRA SODIUM PYROPHOSPHATE, BENZYL ALCOHOL, SODIUM SACCHARIN, PROPYLPARABEN.

LICENSED BY RANIR, LLC. ALL RIGHTS RESERVED. MADE IN INDIA
DIST. BY: ASHTEL STUDIOS, INC., ONTARIO, CA 91761 • COMMENTS OR QUESTIONS?
1-877-274-8358 TOLL FREE IN U.S.A. • 1-909-434-0911 INTERNATIONAL

Q

QUICK CLEAN®

TOOTHPASTE WITH FLUORIDE